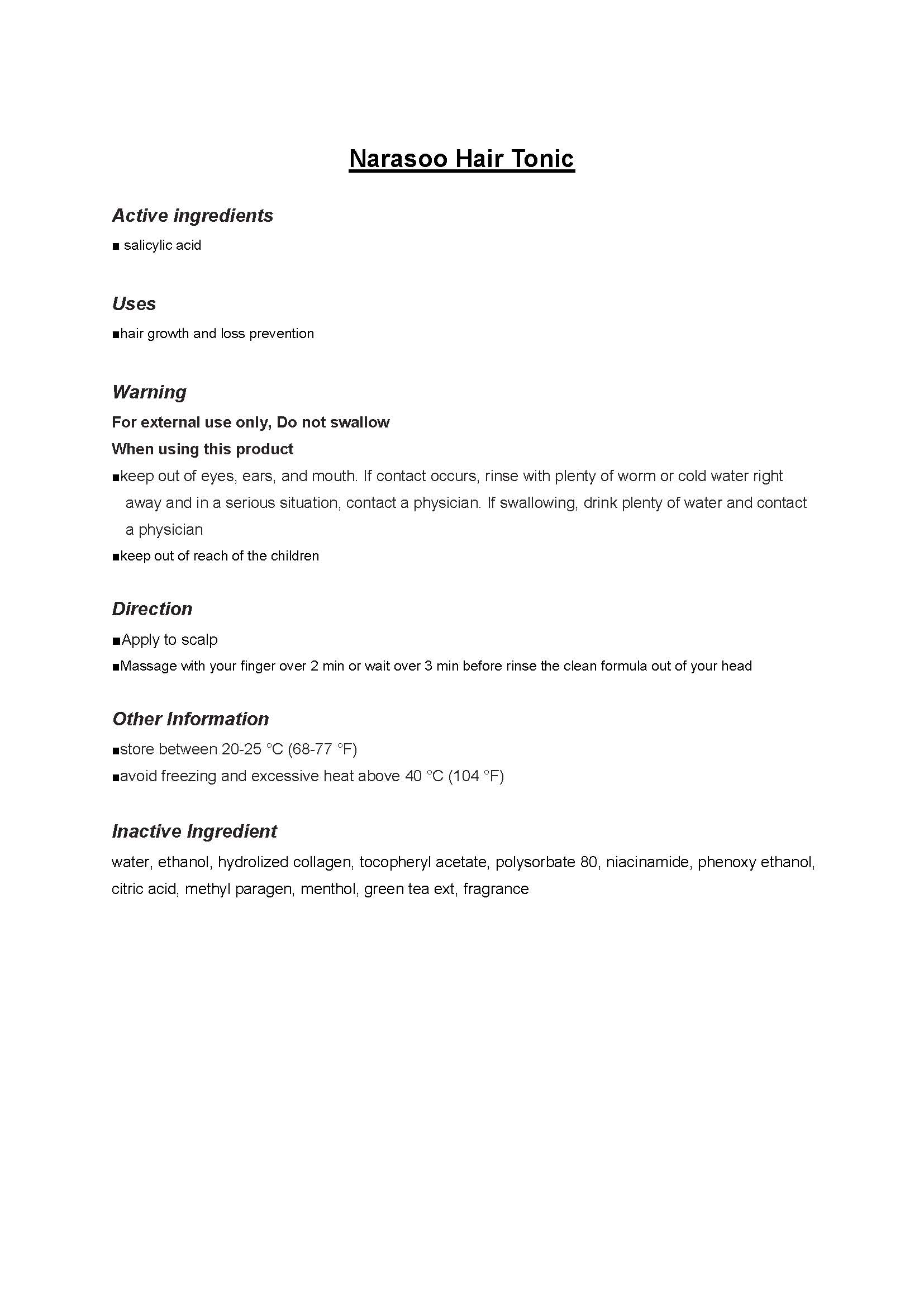 DRUG LABEL: Narasoo Hair Tonic
NDC: 69114-2001 | Form: LIQUID
Manufacturer: RAKU STORY Co., Ltd
Category: otc | Type: HUMAN OTC DRUG LABEL
Date: 20140717

ACTIVE INGREDIENTS: SALICYLIC ACID 0.06 g/1 mL
INACTIVE INGREDIENTS: NIACINAMIDE; MENTHOL; WATER

Drug Facts

ACTIVE INGREDIENT

salicylic acid

INACTIVE INGREDIENT

water, ethanol, hydrolized collagen, tocopheryl acetate, polysorbate 80, niacinamide, phenoxy ethanol, citric acid, methyl paragen, menthol, green tea ext, fragrance

PURPOSE

hair loss prevention and hair grower

keep out of reach of the children

INDICATIONS AND USAGE

apply a proper amount on the scalp and massage with your finger

- do not use the product on wounds or areas with abnomalities such as eczema and inflammation
- storage and handling
make sure to close the lid after use
keep away from children and infants
store away from too high or low temperatures and direct sunlight

DOSAGE AND ADMINISTRATION

for external use only